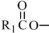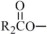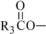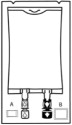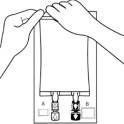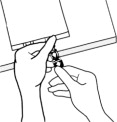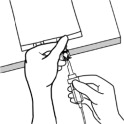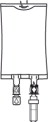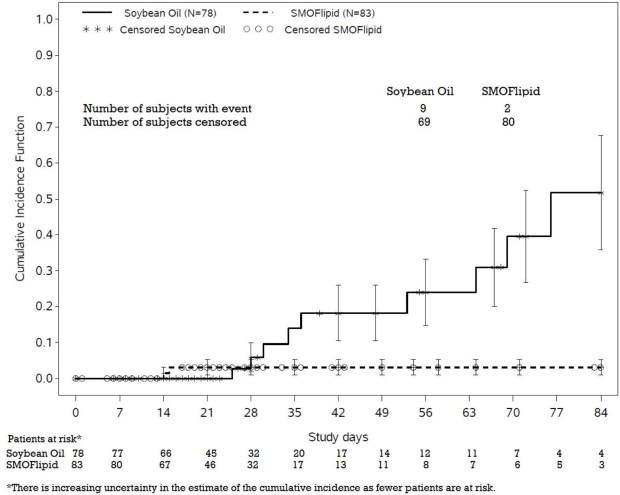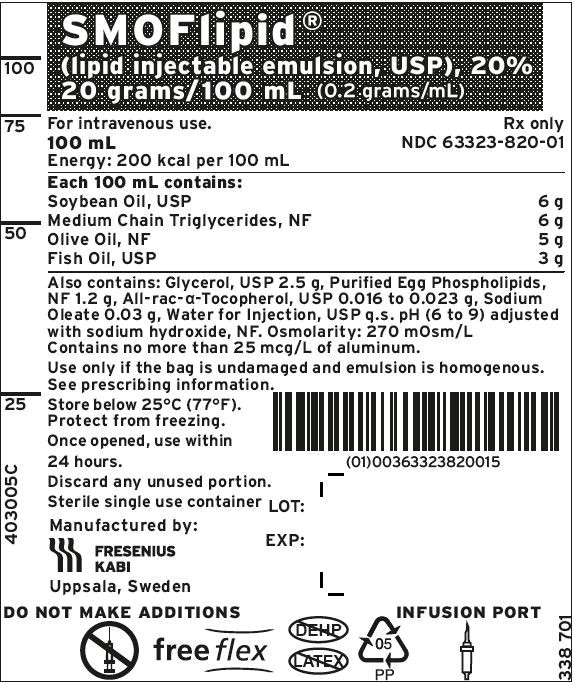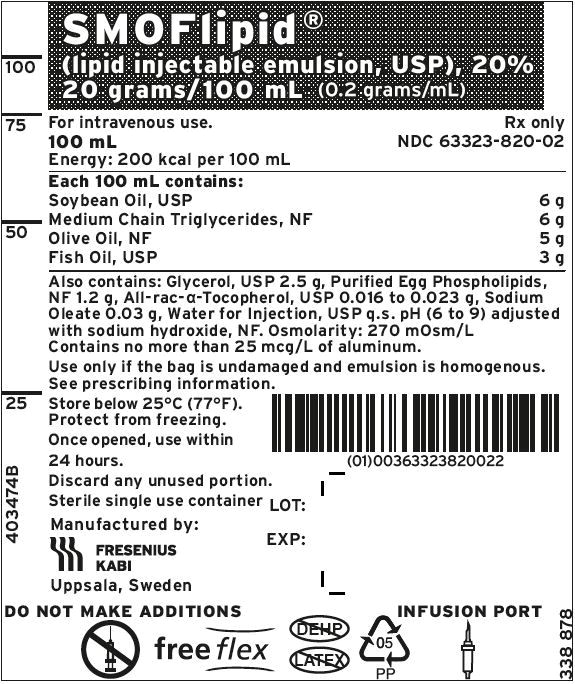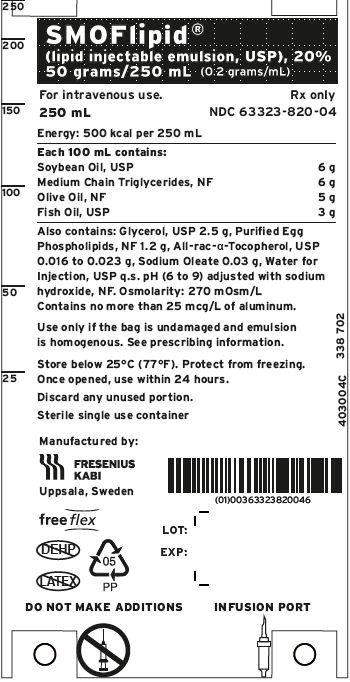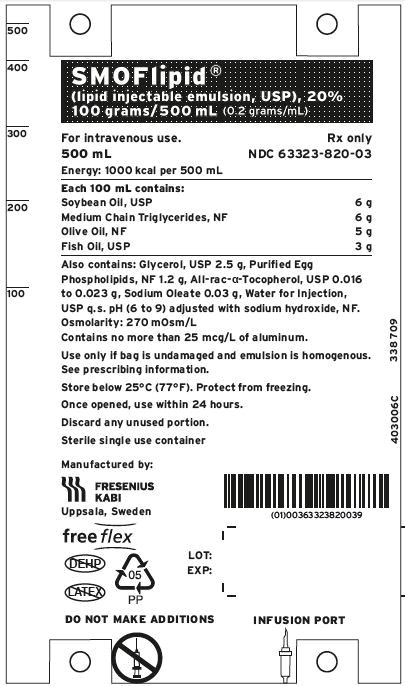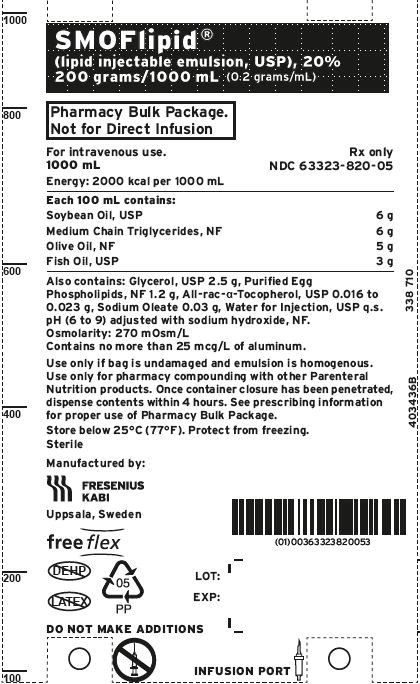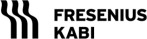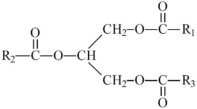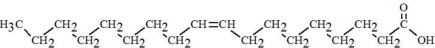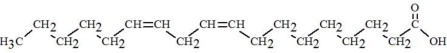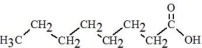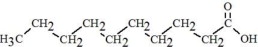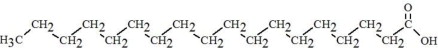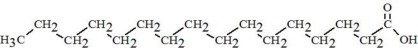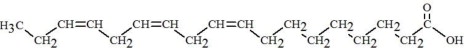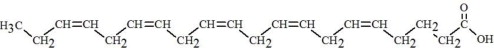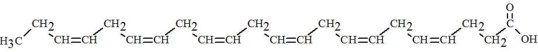 DRUG LABEL: Smoflipid
NDC: 63323-820 | Form: INJECTION, EMULSION
Manufacturer: Fresenius Kabi USA, LLC
Category: prescription | Type: HUMAN PRESCRIPTION DRUG LABEL
Date: 20250815

ACTIVE INGREDIENTS: SOYBEAN OIL 6 g/100 mL; MEDIUM-CHAIN TRIGLYCERIDES 6 g/100 mL; OLIVE OIL 5 g/100 mL; FISH OIL 3 g/100 mL
INACTIVE INGREDIENTS: GLYCERIN; EGG PHOSPHOLIPIDS; .ALPHA.-TOCOPHEROL, DL-; WATER; SODIUM OLEATE; SODIUM HYDROXIDE

HIGHLIGHTS OF PRESCRIBING INFORMATION

These highlights do not include all the information needed to use SMOFLIPID safely and effectively. See full prescribing information for SMOFLIPID.
SMOFLIPID® (lipid injectable emulsion), for intravenous use
Initial U.S. Approval: 2016

RECENT MAJOR CHANGES

Warnings and Precautions (5.3) 7/2025

1 INDICATIONS AND USAGE

SMOFlipid is indicated in adult and pediatric patients, including term and preterm neonates, as a source of calories and essential fatty acids for parenteral nutrition when oral or enteral nutrition is not possible, insufficient, or contraindicated. (1)

2 DOSAGE AND ADMINISTRATION

- For intravenous infusion into a central or peripheral vein. (2.1)
- SMOFlipid Pharmacy Bulk Package is only indicated for use in pharmacy admixture programs for the preparation of three-in-one or total nutrition admixtures. (2.2)
- Protect the admixed PN solution from light. (2.2)
- Recommended dosage depends on age, energy expenditure, clinical status, body weight, tolerance, ability to metabolize and eliminate lipids, and consideration of additional energy given to the patient. (2.3)
- For information on the age-appropriate infusion rate, see the full prescribing information (2.3, 5.1)

Age | Nutritional Requirements
Age | Initial Recommended Dosage | Maximum Dosage
Birth to 2 years of age (including preterm and term neonates) | 0.5 to 1 g/kg/day | 3 g/kg/day
Pediatric patients 2 to <12 years of age | 1 to 2 g/kg/day | 3 g/kg/day
Pediatric patients 12 to 17 years of age | 1 g/kg/day | 2.5 g/kg/day
Adults | 1 to 2 g/kg/day | 2.5 g/kg/day

3 DOSAGE FORMS AND STRENGTHS

SMOFlipid is a sterile, homogenous lipid injectable emulsion supplied as 20 g of lipid/100 mL in 100 mL single-dose Flexible Container, 50 g of lipid/250 mL in 250 mL single-dose Flexible Container, 100 g of lipid/500 mL in 500 mL single-dose Flexible Container, and 200 g of lipid/1000 mL in 1000 mL Pharmacy Bulk Package. (3)

4 CONTRAINDICATIONS

- Known hypersensitivity to fish, egg, soybean, peanut or any of the active or inactive ingredients. (4)
- Severe disorders of lipid metabolism characterized by hypertriglyceridemia (serum triglycerides >1,000 mg/dL). (4, 5.7)

5 WARNINGS AND PRECAUTIONS

- Clinical Decompensation with Rapid Infusion of Intravenous Lipid Emulsion in Neonates and Infants: Acute respiratory distress, metabolic acidosis, and death after rapid infusion of intravenous lipid emulsions have been reported. (5.1, 8.4)
- Parenteral Nutrition-Associated Liver Disease: Increased risk in patients who receive parenteral nutrition for greater than 2 weeks, especially preterm neonates. Monitor liver tests; if abnormalities occur, consider discontinuation or dosage reduction. (5.2, 6.1, 8.4)
- Hypersensitivity Reactions: Monitor for signs or symptoms. Discontinue infusion if reactions occur. (5.3)
- Risk of Infections, Fat Overload Syndrome, Refeeding Syndrome, Hypertriglyceridemia, and Essential Fatty Acid Deficiency: Monitor for signs and symptoms; monitor laboratory parameters. (5.4, 5.5, 5.6, 5.7, 5.9)
- Aluminum Toxicity: Increased risk in patients with renal impairment, including preterm neonates. (5.8, 8.4)

6 ADVERSE REACTIONS

Most common adverse drug reactions (≥5%) from clinical trials in adults were nausea, vomiting, and hyperglycemia. Most common adverse drug reactions (≥5%) from clinical trials in pediatric patients were anemia, vomiting, increased gamma-glutamyltransferase, and nosocomial infection. (6.1)

To report SUSPECTED ADVERSE REACTIONS, contact Fresenius Kabi USA, LLC at 1-800-551-7176 or FDA at 1-800-FDA-1088 or www.fda.gov/medwatch.

7 DRUG INTERACTIONS

Vitamin K Antagonists (e.g., warfarin): Anticoagulant activity may be counteracted; increase monitoring of coagulation parameters. (7)

FULL PRESCRIBING INFORMATION

1 INDICATIONS AND USAGE

SMOFlipid is indicated in adult and pediatric patients, including term and preterm neonates, as a source of calories and essential fatty acids for parenteral nutrition (PN) when oral or enteral nutrition is not possible, insufficient, or contraindicated.

2 DOSAGE AND ADMINISTRATION

2.1 Important Administration Instructions

- SMOFlipid is prepared and administered by a healthcare provider in the inpatient setting. Patients and caregivers may prepare and administer SMOFlipid for home use after appropriate training by a trained healthcare provider.
- SMOFlipid is for intravenous infusion into a central or peripheral vein.
- Do not exceed the recommended maximum infusion rate in Table 1 [see Dosage and Administration (2.3) and Warnings and Precautions (5.1)].
- SMOFlipid admixtures with osmolarity
  ͦ Greater than or equal to 900 mOsm/L must be infused through a central vein.
  ͦ Less than 900 mOsm/L may be administered either through a central or peripheral vein.
- Use a 1.2 micron in-line filter during administration.
- Use a dedicated infusion line without any connections. Do not connect multiple medications in series.
- To prevent air embolism, use a nonvented infusion set or close the vent on a vented set and fully evacuate residual gas in the bag prior to administration.
- Do not pressurize the flexible bag to increase flow rates, and if administration is controlled by a pumping device, turn off the pump before the bag runs dry.
- Do not use infusion sets and lines that contain di-2-ethylhexyl phthalate (DEHP), including infusion sets that contain polyvinyl chloride (PVC) components, because they contain DEHP as a plasticizer.
- SMOFlipid can be infused concurrently into the same vein as dextrose-amino acid solutions (as part of PN) by a Y-connector located near the infusion site; flow rates of each solution should be controlled separately by infusion pumps.
- After connecting the infusion set, start infusion of SMOFlipid immediately. Complete the infusion within 12 hours when using a Y-connector and within 24 hours when used as part of an admixture.

2.2 Preparation Instructions

Use the following instructions to prepare single-dose SMOFlipid 100 mL, 250 mL, and 500 mL Flexible Containers for administration:

1. Inspect Bag
  1. Inspect the integrity indicator (Oxalert®) (A) before removing the overpouch.
  2. Discard the product if the indicator is black, overpouch is opened or damaged, emulsion color is not white, or seals of bag are broken.
2. Remove Overpouch
  1. Place the bag on a clean, flat surface.
  2. Tear overpouch at notch and pull down.
  3. Discard the Oxalert sachet (A) and the oxygen absorber (B).
  4. Visually inspect the bag and contents for particulate matter and discoloration prior to administration. The lipid emulsion should be a homogenous liquid with a milky white appearance. If the mixture is not white or the emulsion has separated (noted by discoloration, phase separation, or oily droplets), or if particulates and/or leakage are observed, discard the bag.
3. Spike Bag
  1. Identify the infusion port (blue cap with the arrow pointing away from the bag).
  2. Immediately before inserting the infusion set, break off the blue infusion port cap.
  3. Use infusion sets according to ISO Number 8536-4 with an external spike diameter of 5.5 to 5.7 mm and use a nonvented infusion set or close the air-inlet on a vented set.
  4. Use a 1.2 micron in-line filter for administration.
  5. Hold the base of the infusion port.
  6. Insert the spike through the infusion port by rotating your wrist slightly until the spike is inserted.
  7. Do not pierce the infusion port more than once.
4. Hang the bag
  1. On the hanger cut and start infusion.
  2. Discard unused portion.

SMOFlipid 100 mL, 250 mL and 500 mL single-dose Flexible Containers

- After removing the overpouch, infuse immediately. If not used immediately, the product should be stored at 2°C to 8°C (36°F to 46°F) for no longer than 24 hours. After removal from storage, infuse within 12 hours when using a Y-connector and within 24 hours when used as part of an admixture.

SMOFlipid 1000 mL Pharmacy Bulk Package

- For admixing use only and not for direct intravenous infusion. Prior to administration, transfer to a separate PN container for individual patient use.
- Transfer the contents through the blue infusion port using a suitable sterile transfer device or dispensing set. Discard any unused contents.
- Use the Pharmacy Bulk Package immediately for admixing after removal from overpouch. If not used immediately, the product can be stored for no longer than 24 hours at 2°C to 8°C (36°F to 46°F). After removal from storage, and once the closure is penetrated, use Pharmacy Bulk Package contents within 4 hours.

Admixing Instructions

- Prepare the admixture in PN containers using strict aseptic techniques to avoid microbial contamination.
- Do not add SMOFlipid to the PN container first; destabilization of the lipid may occur. The prime destabilizers of emulsions are excessive acidity (such as a pH <5) and inappropriate electrolyte content. Amino acid solutions exert buffering effects that protect the emulsion from destabilization. Give careful consideration to the addition of divalent cations (Ca^++ and Mg^++), which have been shown to cause emulsion instability.
- Do not inject additives directly into SMOFlipid.
- SMOFlipid may be mixed with amino acid and dextrose injections to produce “all-in-one” PN admixtures. The mixing sequence below must be followed for manual compounding to minimize pH-related problems by ensuring that typically acidic dextrose injections are not mixed with lipid emulsions alone; shake bags gently after each addition.
  ͦ Transfer dextrose injection to the PN container.
  ͦ Transfer amino acid injection.
  ͦ Transfer SMOFlipid.
- Simultaneous transfer of amino acid injection, dextrose injection, and SMOFlipid to the PN container is also permitted; follow automated compounding device instructions as indicated. Use gentle agitation during admixing to minimize localized concentration effects.
- Additions to the PN admixtures should be evaluated by a pharmacist for compatibility. Questions about compatibility may be directed to Fresenius Kabi USA, LLC.
- Inspect the admixture to ensure that precipitates have not formed during preparation of the admixture and the emulsion has not separated. Discard the admixture if any of the above are observed.
- Infuse admixtures containing SMOFlipid immediately. If not used immediately, store admixtures under refrigeration at 2°C to 8°C (36°F to 46°F) for no longer than 24 hours. Infusion must be complete within 24 hours after removal from refrigeration. Discard any remaining admixture.
- Protect the admixed PN solution from light.

2.3 Recommended Dosage and Administration

- The recommended nutritional requirements of lipid and recommended dosages of SMOFlipid to be administered to meet those requirements for pediatric and adult patients are provided in Table 1, along with recommendations for the initial and maximum infusion rates.
- The recommended duration of infusion for SMOFlipid will vary depending on the clinical situation. Adjust the administration flow rate by taking into account the dose being administered, the daily volume/intake, and the duration of the infusion [see Overdosage (10)].
- When determining dose, energy supplied by dextrose and amino acids from PN, as well as energy from oral or enteral nutrition, has to be taken into account. Energy and lipid provided from lipid-based medications should also be taken into account (e.g., propofol).
- Prior to administration of SMOFlipid, correct severe fluid and electrolyte disorders and measure serum triglyceride levels to establish a baseline value. In patients with elevated triglyceride levels, initiate SMOFlipid at a lower dosage and titrate in smaller increments, monitoring the triglyceride levels with each adjustment [see Warnings and Precautions (5.7)].
- SMOFlipid contains 0.162 to 0.225 mg/mL of all-rac-alpha-tocopherol. Take into account the amount of all-rac-alpha-tocopherol in SMOFlipid when determining the need for additional supplementation.

Table 1: Recommended Pediatric and Adult Dosage and Infusion Rate
Age | Nutritional Requirements | Direct Infusion Rate
Age | Recommended Initial Dosage and Maximum Dosage | Initial | Maximum
Birth to 2 years of age (including preterm and term neonates*) [see Warnings and Precautions (5.1)] | Initial 0.5 to 1 g/kg/day not to exceed 3 g/kg/day** | 0.1 to 0.2 mL/kg/hour for the first 15 to 30 minutes; gradually increase to the required rate after 30 minutes | 0.75 mL/kg/hour
Pediatric patients 2 to <12 years of age | Initial 1 to 2 g/kg/day not to exceed 3 g/kg/day** | 0.2 to 0.4 mL/kg/hour for the first 15 to 30 minutes; gradually increase to the required rate after 30 minutes | 0.75 mL/kg/hour
Pediatric patients 12 to 17 years of age | Initial 1 g/kg/day not to exceed 2.5 g/kg/day** | 0.2 to 0.4 mL/kg/hour for the first 15 to 30 minutes; gradually increase to the required rate after 30 minutes | 0.75 mL/kg/hour
Adults | 1 to 2 g/kg/day not to exceed 2.5 g/kg/day** | 0.2 mL/kg/hour for the first 15 to 30 minutes; gradually increase to the required rate after 30 minutes | 0.5 mL/kg/hour
*The neonatal period is defined as including term, post-term, and preterm newborn infants. The neonatal period for term and post-term infants is the day of birth plus 27 days. For preterm infants, the neonatal period is defined as the day of birth through the expected age of delivery plus 27 days (i.e., 44 weeks post-menstrual age).
** Daily dosage should also not exceed a maximum of 60% of total energy requirements [see Overdosage (10)].

3 DOSAGE FORMS AND STRENGTHS

SMOFlipid is a sterile, homogenous lipid injectable emulsion in Flexible Containers supplied as:

- 20 g of lipid/100 mL in 100 mL single-dose Flexible Container
- 50 g of lipid/250 mL in 250 mL single-dose Flexible Container
- 100 g of lipid/500 mL in 500 mL single-dose Flexible Container
- 200 g of lipid/1000 mL in 1000 mL Pharmacy Bulk Package

4 CONTRAINDICATIONS

Use of SMOFlipid is contraindicated in patients with:

- Known hypersensitivity to fish, egg, soybean, peanut or any of the active or inactive ingredients in SMOFlipid [see Warnings and Precautions (5.3)]
- Severe disorders of lipid metabolism characterized by hypertriglyceridemia (serum triglyceride >1,000 mg/dL) [see Warnings and Precautions (5.7)]

5 WARNINGS AND PRECAUTIONS

5.1 Clinical Decompensation with Rapid Infusion of Intravenous Lipid Emulsion in Neonates and Infants

In the postmarketing setting, serious adverse reactions including acute respiratory distress, metabolic acidosis, and death have been reported in neonates and infants after rapid infusion of intravenous lipid emulsions. Hypertriglyceridemia was commonly reported.

Strictly adhere to the recommended total daily dosage; the hourly infusion rate should not exceed 0.75 mL/kg/hour [see Dosage and Administration (2.3)].

Preterm and small for gestational age infants have poor clearance of intravenous lipid emulsion and increased free fatty acid plasma levels following lipid emulsion infusion.

Carefully monitor the infant's ability to eliminate the infused lipids from the circulation (e.g., measure serum triglycerides and/or plasma free fatty acid levels). If signs of poor clearance of lipids from the circulation occur, stop the infusion and initiate a medical evaluation [see Warnings and Precautions (5.5, 5.7) and Overdosage (10)].

5.2 Parenteral Nutrition-Associated Liver Disease and Other Hepatobiliary Disorders

Risk of Parenteral Nutrition-Associated Liver Disease

Parenteral nutrition-associated liver disease (PNALD), also referred to as intestinal failure- associated liver disease (IFALD), can present as cholestasis or hepatic steatosis, and may progress to steatohepatitis with fibrosis and cirrhosis (possibly leading to chronic hepatic failure). The etiology of PNALD is multifactorial; however, intravenously administered phytosterols (plant sterols) contained in plant-derived lipid emulsions, including SMOFlipid, have been associated with development of PNALD.

In a randomized study of neonates and infants expected to be treated with PN for at least 28 days, parenteral nutrition-associated cholestasis (PNAC), a precursor to PNALD, developed less frequently in SMOFlipid-treated patients than in 100% soybean oil lipid emulsion-treated patients [see Adverse Reactions (6.1), Use in Specific Populations (8.4)].

Monitor liver tests in patients treated with SMOFlipid and consider discontinuation or dosage reduction if abnormalities occur.

Other Hepatobiliary Disorders

Hepatobiliary disorders including cholecystitis and cholelithiasis have developed in some PN- treated patients without preexisting liver disease.

Monitor liver tests when administering SMOFlipid. Patients developing signs of hepatobiliary disorders should be assessed early to determine whether these conditions are related to SMOFlipid use.

5.3 Hypersensitivity Reactions

SMOFlipid contains soybean oil, fish oil, and egg phospholipids, which may cause hypersensitivity reactions. Cross reactions have been observed between soybean and peanut. In postmarketing experience, anaphylaxis has been reported following SMOFlipid administration [see Adverse Reactions (6.2)].

SMOFlipid is contraindicated in patients with known hypersensitivity to fish, egg, soybean, peanut or any of the active or inactive ingredients in SMOFlipid [see Contraindications (4)]. If a hypersensitivity reaction occurs, stop infusion of SMOFlipid immediately and initiate appropriate treatment and supportive measures.

5.4 Infections

Lipid emulsions, such as SMOFlipid, can support microbial growth and are an independent risk factor for the development of catheter-related bloodstream infections. To decrease the risk of infectious complications, ensure aseptic techniques are used for catheter placement, catheter maintenance, and preparation and administration of SMOFlipid.

Monitor for signs and symptoms of infection including fever and chills, as well as laboratory test results that might indicate infection (including leukocytosis and hyperglycemia). Perform frequent checks of the intravenous catheter insertion site for edema, redness, and discharge.

5.5 Fat Overload Syndrome

Fat overload syndrome is a rare condition that has been reported with intravenous lipid injectable emulsions and is characterized by a sudden deterioration in the patient's condition (e.g., fever, anemia, leukopenia, thrombocytopenia, coagulation disorders, hyperlipidemia, hepatomegaly, deteriorating liver function, and central nervous system manifestations such as coma). A reduced or limited ability to metabolize lipids, accompanied by prolonged plasma clearance (resulting in higher lipid levels), may result in this syndrome. Although fat overload syndrome has been most frequently observed when the recommended lipid dose or infusion rate was exceeded, cases have also been described when the lipid formulation was administered according to instructions.

If signs or symptoms of fat overload syndrome occur, stop SMOFlipid. The syndrome is usually reversible when the infusion of the lipid emulsion is stopped.

5.6 Refeeding Syndrome

Administering PN to severely malnourished patients may result in refeeding syndrome, which is characterized by the intracellular shift of potassium, phosphorus, and magnesium as patients become anabolic. Thiamine deficiency and fluid retention may also develop. To prevent these complications, closely monitor severely malnourished patients and slowly increase their nutrient intake.

5.7 Hypertriglyceridemia

The use of SMOFlipid is contraindicated in patients with hypertriglyceridemia with serum triglyceride concentrations >1,000 mg/dL.

Patients with conditions such as inherited lipid disorders, obesity, diabetes mellitus, or metabolic syndromes have a higher risk of developing hypertriglyceridemia with the use of SMOFlipid. In addition, patients with hypertriglyceridemia may have worsening of their hypertriglyceridemia with administration of SMOFlipid. Excessive dextrose administration may further increase such risk.

Evaluate patients' capacity to metabolize and eliminate the infused lipid emulsion by measuring serum triglycerides before the start of infusion (baseline value) and regularly throughout treatment. If triglyceride levels are above 400 mg/dL in adults, stop the SMOFlipid infusion and monitor serum triglyceride levels to avoid clinical consequences of hypertriglyceridemia such as pancreatitis. In pediatric patients with hypertriglyceridemia, lower triglyceride levels (i.e., below 400 mg/dL) may be associated with adverse reactions. Monitor serum triglyceride levels to avoid potential complications with hypertriglyceridemia such as pancreatitis, lipid pneumonitis, and neurologic changes, including kernicterus.

To minimize the risk of new or worsening of hypertriglyceridemia, assess high-risk patients for their overall energy intake including other sources of lipids and dextrose, as well as concomitant drugs that may affect lipid and dextrose metabolism.

5.8 Aluminum Toxicity

SMOFlipid contains no more than 25 mcg/L of aluminum. Prolonged PN administration in patients with renal impairment may result in aluminum reaching toxic levels. Preterm neonates are at greater risk because their kidneys are immature and they require large amounts of calcium and phosphate solutions that contain aluminum.

Patients with impaired kidney function, including preterm neonates, who receive parenteral levels of aluminum at greater than 4 to 5 mcg/kg/day can accumulate aluminum at levels associated with central nervous system and bone toxicity. Tissue loading in these patients may occur at even lower rates of administration.

5.9 Essential Fatty Acid Deficiency

Treatment-emergent cases of moderate or severe essential fatty acid deficiency (EFAD) (defined as the triene [Mead acid] to tetraene [arachidonic acid] ratio >0.2 and >0.4, respectively) were not observed in pediatric clinical trials of SMOFlipid up to 28 days [see Adverse Reactions (6.1)].

However, cases of EFAD have been reported in adult and pediatric patients in the postmarketing period with the use of SMOFlipid. The median time to onset was greater than 28 days among cases that reported time to onset.

Monitor patients for laboratory evidence (e.g., abnormal fatty acid levels) and clinical symptoms of EFAD (e.g., skin manifestations, poor growth). Laboratory testing using the triene to tetraene ratio may not be adequate to diagnose EFAD, and assessment of individual fatty acid levels may be needed. Ensure patients are receiving recommended dosages of SMOFlipid to prevent EFAD [see Dosage and Administration (2.3), Description (11)].

5.10 Monitoring/Laboratory Tests

Throughout treatment, monitor serum triglycerides [see Warnings and Precautions (5.7)], fluid and electrolyte status, blood glucose, liver and kidney function, coagulation parameters, and complete blood count including platelets.

The lipids contained in SMOFlipid may interfere with some laboratory blood tests (e.g., hemoglobin, lactate dehydrogenase, bilirubin, oxygen saturation) if blood is sampled before lipids have cleared from the bloodstream. Conduct these blood tests at least 6 hours after stopping the infusion.

SMOFlipid contains vitamin K that may counteract anticoagulant activity [see Drug Interactions (7)].

6 ADVERSE REACTIONS

Adverse reactions described elsewhere in this Prescribing Information are:

- Clinical Decompensation with Rapid Infusion of Intravenous Lipid Emulsion in Neonates and Infants [see Warnings and Precautions (5.1)]
- Parenteral Nutrition-Associated Liver Disease and Other Hepatobiliary Disorders [see Warnings and Precautions (5.2)]
- Hypersensitivity Reactions [see Warnings and Precautions (5.3)]
- Infections [see Warnings and Precautions (5.4)]
- Fat Overload Syndrome [see Warnings and Precautions (5.5)]
- Refeeding Syndrome [see Warnings and Precautions (5.6)]
- Hypertriglyceridemia [see Warnings and Precautions (5.7)]
- Aluminum Toxicity [see Warnings and Precautions (5.8)]
- Essential Fatty Acid Deficiency [see Warnings and Precautions (5.9)]

6.1 Clinical Trials Experience

Because clinical trials are conducted under widely varying conditions, adverse reaction rates observed in the clinical trials of a drug cannot be compared to rates in the clinical trials of another drug and may not reflect the rates observed in clinical practice.

The safety database for SMOFlipid includes exposure in 399 patients (229 adults; 170 pediatric) in 9 clinical trials. Adult patients were exposed for 5 days to 4 weeks in 5 clinical trials. The pooled population exposed to SMOFlipid was adult patients up to 89 years old (20 to 89 years of age), 43% female and 99% Caucasian. The most frequently reported medical histories in the SMOFlipid group were surgical and medical procedures (84%), neoplasms (57%), gastrointestinal disorders (53%), vascular disorders (37%), and infections and infestations (20%). SMOFlipid was used as a component of PN which also included dextrose, amino acids, vitamins, and trace elements. Two of the 5 studies in adults were performed with SMOFlipid as a component of PN delivered in a 3- chamber bag.

Table 2: Adverse Reactions in >1% of Adult Patients Treated with SMOFlipid
Adverse Reaction | Number of Patients in SMOFlipid Group (N=229) | Number of Patients in Soybean Oil lipid emulsion Comparator Group (N=230)
Nausea | 20 (9%) | 26 (11%)
Vomiting | 15 (7%) | 12 (5%)
Hyperglycemia | 12 (5%) | 5 (2%)
Flatulence | 10 (4%) | 4 (2%)
Pyrexia | 9 (4%) | 11 (5%)
Abdominal pain | 8 (4%) | 5 (2%)
Blood triglycerides increased | 6 (3%) | 4 (2%)
Hypertension | 6 (3%) | 9 (4%)
Sepsis | 5 (2%) | 4 (2%)
Dyspepsia | 5 (2%) | 1 (0%)
Urinary tract infection | 4 (2%) | 3 (1%)
Anemia | 4 (2%) | 2 (1%)
Device related infection | 4 (2%) | 2 (1%)

Less common adverse reactions occurring in ≤1% of adult patients who received SMOFlipid were dyspnea, leukocytosis, diarrhea, pneumonia, cholestasis, dysgeusia, increased blood alkaline phosphatase, increased gamma-glutamyltransferase, increased C-reactive protein, tachycardia, liver function test abnormalities, headache, pruritus, dizziness, rash and thrombophlebitis.

The 170 patients treated with SMOFlipid in four pediatric trials consisted of 149 patients <28 days of age, 13 patients 28 days to <2 years of age, and 8 patients 2 to 7 years of age; the duration of exposure was 7 to 84 days. Forty five percent of the pediatric patients were female, and 89% were Caucasian. Most pediatric patients were preterm neonates with feeding intolerance or other conditions requiring short-term (<29 days) PN.

Table 3: Adverse Reactions in >1% of Pediatric Patients Treated with SMOFlipid
Adverse Reaction | Number of Patients in SMOFlipid Group (N=170) | Number of Patients in Soybean Oil lipid emulsion Comparator Group (N=163)
Anemia | 30 (18%) | 33 (20%)
Vomiting | 16 (9%) | 16 (10%)
Gamma-glutamyltransferase increased | 10 (6%) | 12 (7%)
Nosocomial infection | 10 (6%) | 6 (4%)
Cholestasis | 7 (4%) | 10 (6%)
Pyrexia | 7 (4%) | 7 (4%)
C-reactive protein increased | 6 (4%) | 7 (4%)
Hyperbilirubinemia | 5 (3%) | 7 (4%)
Abdominal pain | 4 (2%) | 5 (3%)
Bilirubin conjugated increased | 3 (2%) | 7 (4%)
Diarrhea | 3 (2%) | 4 (3%)
Tachycardia | 3 (2%) | 4 (3%)
Thrombocytopenia | 3 (2%) | 4 (3%)
Hyperglycemia | 3 (2%) | 2 (1%)
Sepsis | 3 (2%) | 2 (1%)

Less common adverse reactions occurring in ≤1% of pediatric patients who received SMOFlipid were decreased hematocrit, metabolic acidosis, increased blood triglycerides, infection, increased blood alkaline phosphatase, increased alanine aminotransferase, fluid overload, hypertension, hypertriglyceridemia, and rash.

The hepatic safety of SMOFlipid was evaluated in Pediatric Study 1, a randomized, active- controlled, double-blind, parallel-group, multi-center study that included 152 neonates and

9 patients ranging in age from 29 to 153 days who were expected to require PN for at least 28 days.

PNAC (defined as direct bilirubin >2mg/dl with a second confirmed elevation >2mg/dl at least 7 days later) occurred in 2.4% (2/83) of SMOFlipid-treated patients and 11.5% (9/78) in soybean oil lipid emulsion-treated patients. Most PNAC events occurred in patients who were treated for longer than 28 days.

The estimated cumulative incidence of PNAC is shown in the Kaplan-Meier cumulative incidence curve in Figure 1 [see Clinical Trials (14)].

Figure 1 Cumulative Incidence Curve of Time to Parenteral Nutrition-Associated Cholestasis (PNAC) with Standard Error Bars

In the same trial, EFAD was determined by calculating the Holman index (the triene [Mead acid] to tetraene [arachidonic acid] ratio; T:T ratio). At the end of the first 28 days of treatment, 2.4% (2/83) SMOFlipid-treated patients and 2.6% (2/78) soybean oil lipid emulsion-treated patients had suspected EFAD (T:T ratio >0.05), and there were no cases of moderate (T:T ratio >0.2) or severe (T:T ratio >0.4) EFAD. There are insufficient data from this trial to determine the incidence of EFAD with duration of SMOFlipid treatment greater than 28 days because of substantial patient discontinuation from PN during the first 28 days.

6.2 Postmarketing Experience

The following adverse reactions have been identified during post-approval use of SMOFlipid in countries where it is registered. Because these reactions are reported voluntarily from a population of uncertain size, it is not always possible to reliably estimate their frequency or establish a causal relationship to product exposure.

Cardiac disorders: palpitations

General disorders and administration site conditions: chills, chest pain, malaise

Hepatobiliary disorders: cholestasis

Infections and infestations: infection

Metabolism and nutrition disorders: fatty acid deficiency

Respiratory, thoracic and mediastinal disorders: dyspnea

Immune system disorders: hypersensitivity reactions, including anaphylaxis [see Contraindications (4), Warnings and Precautions (5.3)]

Skin and subcutaneous tissue disorders: hyperhidrosis

Vascular disorders: phlebitis

7 DRUG INTERACTIONS

Soybean and olive oils in SMOFlipid contain vitamin K1 which may counteract the anticoagulant activity of vitamin K antagonists such as warfarin. In patients who receive concomitant SMOFlipid and warfarin, increase monitoring of laboratory parameters for anticoagulant activity.

8 USE IN SPECIFIC POPULATIONS

8.1 Pregnancy

Risk Summary

Administration of the recommended dose of SMOFlipid is not expected to cause major birth defects, miscarriage, or other adverse maternal or fetal outcomes. No animal reproduction studies have been conducted with SMOFlipid. There are risks to the fetus associated with severe malnutrition during pregnancy (see Clinical Considerations).

The estimated background risk of major birth defects and miscarriage for the indicated population(s) is unknown. All pregnancies have a background risk of birth defect, loss, or other adverse outcomes. In the U.S. general population, the estimated background risk of major birth defects and miscarriage in clinically recognized pregnancies is 2% to 4% and 15% to 20%, respectively.

Clinical Considerations

Disease-Associated Maternal and/or Embryo-Fetal Risk

Severe malnutrition in pregnant women is associated with preterm delivery, low birth weight, intrauterine growth restriction, congenital malformations, and perinatal mortality. Parenteral nutrition should be considered if the pregnant woman's nutritional requirements cannot be fulfilled by oral or enteral intake.

8.2 Lactation

Risk Summary

Administration of the recommended dose of SMOFlipid is not expected to cause harm to a breastfed infant. There are no data on the presence of SMOFlipid in human or animal milk or its effects on milk production. Available published literature includes fewer than five reported cases of breastfed infants exposed to various lipid emulsions via lactation, and these cases did not report adverse events. The developmental and health benefits of breastfeeding should be considered along with the mother's clinical need for SMOFlipid and any potential adverse effects of SMOFlipid on the breastfed infant, or from the underlying maternal condition.

8.4 Pediatric Use

The safety and effectiveness of SMOFlipid have been established as a source of calories and essential fatty acids for PN when oral or enteral nutrition is not possible, insufficient, or contraindicated in pediatric patients, including term and preterm neonates. Use of SMOFlipid in neonates is supported by evidence from short-term (i.e., 1- to 4- week) studies, and one study following neonates beyond 4 weeks [see Clinical Studies (14.2)]. Use of SMOFlipid in older pediatric patients is supported by evidence from a short-term (i.e., <28 days) study in pediatric patients 28 days to 12 years of age and additional evidence from studies in adults [see Clinical Studies (14)]. The most common adverse reactions in SMOFlipid-treated pediatric patients were anemia, vomiting, gamma-glutamyltransferase increased, and nosocomial infection [see Adverse Reactions (6.1)].

PNALD, also referred to as IFALD, has been reported in pediatric patients who received SMOFlipid for more than 2 weeks. PNAC (a precursor to PNALD) was reported less frequently in SMOFlipid- treated patients compared to soybean oil lipid emulsion-treated patients in Pediatric Study 1 [see Warnings and Precautions (5.2) and Adverse Reactions (6.1)]. Although clinically significant cases of EFAD were not observed during short-term use in pediatric clinical studies, cases of EFAD have been reported with the use of SMOFlipid in the postmarketing setting [see Warnings and Precautions (5.9), Adverse Reactions (6.1)]. Monitor pediatric patients for laboratory evidence of EFAD because they may be particularly vulnerable to neurologic complications if adequate amounts of essential fatty acids are not provided [see Warnings and Precautions (5.9)].

In the postmarketing setting, clinical decompensation with rapid infusion of intravenous lipid emulsion in neonates and infants, sometimes fatal, has been reported [see Warnings and Precautions (5.1)]. Because of immature renal function, preterm infants receiving prolonged treatment with SMOFlipid may be at risk for aluminum toxicity [see Warnings and Precautions (5.8)].

8.5 Geriatric Use

Energy expenditure and requirements may be lower for older adults than younger patients. Of the 354 adult patients in clinical studies of SMOFlipid, 35% were >65 years of age and 10% were >75 years of age. No overall differences in the safety and efficacy of SMOFlipid were observed between these patients and younger patients, and other reported clinical experience has not identified differences in responses between the elderly and younger patients, but greater sensitivity in some older patients cannot be ruled out.

10 OVERDOSAGE

In the event of an overdose, serious adverse reactions may result [see Warnings and Precautions (5.1, 5.5)]. Stop the infusion of SMOFlipid until triglyceride levels have normalized and symptoms have abated. The effects are usually reversible by stopping the lipid infusion. If medically appropriate, further intervention may be indicated. Lipids are not dialyzable from plasma.

11 DESCRIPTION

SMOFlipid is a sterile, nonpyrogenic, white, homogenous lipid emulsion for intravenous infusion. The lipid content of SMOFlipid is 0.2 g/mL, and comprises a mixture of soybean oil, MCTs, olive oil, and fish oil. The mean concentration of linoleic acid (an omega-6 essential fatty acid) is 35 mg/mL (range of 28 to 50 mg/mL), and alpha-linolenic acid (an omega-3 essential fatty acid) is 4.5 mg/mL (range of 3 to 7 mg/mL). The phosphate content is 15 mmol/L.

The total energy content, including fat, phospholipids, and glycerol is 2,000 kcal/L.

Each 100 mL of SMOFlipid contains approximately 6 g soybean oil, 6 g MCT, 5 g olive oil, 3 g fish oil, 1.2 g egg phospholipids, 2.5 g glycerin, 16.3 to 22.5 mg all-rac-alpha-tocopherol, 0.03 g sodium oleate, water for injection, and sodium hydroxide for pH adjustment (pH 6 to 9).

SMOFlipid has an osmolality of approximately 380 mOsm/kg water (which represents an osmolarity of 270 mOsm/L).

The oils included in SMOFlipid consist of a mixture of triglycerides of predominantly unsaturated fatty acids with the following structure:

where , , and are saturated and unsaturated fatty acid residues. The major components of the fatty acids in SMOFlipid are oleic acid (23% to 35%), linoleic acid (14% to 25%), caprylic acid (13% to 24%), palmitic acid (7% to 12%), capric acid (5% to 15%), stearic acid (1.5% to 4%), alpha-linolenic acid (1.5% to 3.5%), eicosapentaenoic acid (EPA; 1% to 3.5%), and docosahexaenoic acid (DHA; 1% to 3.5%).

Oleic Acid C18H34O2

Linoleic Acid C18H32O2

Caprylic Acid C8H16O2

Capric Acid C10H20O2

Stearic Acid C18H36O2

Palmitic Acid C16H32O2

Linolenic Acid C18H30O2

EPA C20H30O2

DHA C22H32O2

SMOFlipid contains no more than 25 mcg/L of aluminum.

The container is not made with natural rubber latex, PVC, or DEHP.

12 CLINICAL PHARMACOLOGY

12.1 Mechanism of Action

SMOFlipid provides a biologically utilizable source of calories and essential fatty acids.

Fatty acids serve as an important substrate for energy production. The most common mechanism of action for energy production derived from fatty acid metabolism is beta oxidation. Fatty acids are also important for membrane structure and function, as precursors for bioactive molecules (such as prostaglandins), and as regulators of gene expression.

12.2 Pharmacodynamics

The pharmacodynamic effects of SMOFlipid have not been fully characterized.

12.3 Pharmacokinetics

SMOFlipid provides fatty acids in the form of triglycerides which are hydrolyzed by lipoprotein lipase to release free fatty acids. Alpha-linolenic acid and linoleic acid are metabolized within a common biochemical pathway through a series of desaturation and elongation steps. Downstream products of alpha-linolenic acid are EPA and DHA, and linoleic acid is converted to arachidonic acid.

13 NONCLINICAL TOXICOLOGY

13.1 Carcinogenesis, Mutagenesis, Impairment of Fertility

Studies with SMOFlipid have not been performed to evaluate the carcinogenic potential or effects on fertility.

No mutagenic effects were observed in the following in vitro studies with SMOFlipid: bacterial gene mutation assay in Salmonella typhimurium, chromosomal aberration assay in human lymphocytes, and hypoxanthine phosphoribosyl transferase (HPRT) gene mutation assay in V79 cells.

In an in vivo bone marrow cytogenic study in rats, no mutagenic effect was observed.

14 CLINICAL STUDIES

14.1 Adult Clinical Studies

The efficacy of SMOFlipid compared to soybean oil lipid emulsions was evaluated in 3 clinical studies in adult patients. Nutritional efficacy in adult studies was assessed by changes in anthropometric indices (body weight, height, and body mass index [BMI]), changes in lipid and protein metabolism (albumin), and fatty acid parameters. Of the 354 adult patients (176 SMOFlipid; 178 comparator), 62% were male, 99% were Caucasian, and ages ranged from 19 to 96 years. All patients received SMOFlipid or the comparator as part of a PN regimen. Although Adult Study 1, Adult Study 2, and Adult Study 3 were not adequately designed to demonstrate the noninferiority of SMOFlipid to the soybean oil comparator, they support SMOFlipid as a source of calories and essential fatty acids in adults. The lipid dosage was variable in these studies and adjusted to the patient's nutritional requirements.

Adult Study 1 was a double-blind, randomized, active-controlled, parallel-group, multicenter study in patients who required PN for at least 28 days. Seventy-five patients were enrolled, and 73 patients were treated with either SMOFlipid or a soybean oil lipid emulsion. Changes in mean triglyceride levels from baseline values to Week 4 were similar in both the SMOFlipid and comparator groups. Mean albumin levels demonstrated a comparable decrease in both groups. Mean changes in body weight (kg) and BMI (kg/m^2) were similar in both the SMOFlipid and comparator group.

Adult Study 2 was a phase 3, randomized, double-blind, active-controlled, multicenter study. A total of 249 postoperative adult patients were randomized to receive either SMOFlipid or a soybean oil intravenous lipid emulsion for at least 5 days as part of their total parenteral nutrition (TPN) regimen. From baseline to Day 6, mean triglyceride levels increased similarly in both the SMOFlipid and comparator groups.

Adult Study 3 was a double-blind randomized, active-controlled, parallel-group, single-center study in 32 adult patients who required TPN for 10 to 14 days. Patients were treated with either SMOFlipid or a soybean oil lipid emulsion. The increase in mean triglyceride levels from baseline to the final assessment was similar in both the SMOFlipid and comparator groups.

14.2 Pediatric Clinical Studies

The efficacy of SMOFlipid compared to soybean oil lipid emulsions in pediatric patients of all age groups, including term and preterm neonates, was evaluated in 333 pediatric patients in 4 randomized active-controlled, double-blind, parallel-group controlled clinical studies. Although Pediatric Studies 1, 2, 3, and 4 were not adequately designed to demonstrate the noninferiority of SMOFlipid to the soybean oil comparator, they support SMOFlipid as a source of calories and essential fatty acids in pediatric patients. The 333 pediatric patients (170 SMOFlipid; 163 comparator) consisted of 296 patients who were <28 days old, 22 patients 29 days to <2 years old, and 15 patients 2 to <12 years old. Fifty percent of the pediatric patients were male and 87% were Caucasian. All patients received SMOFlipid or the comparator as part of a PN regimen. Nutritional efficacy in neonates was assessed by changes in anthropometric indices (body weight, height, head circumference). Nutritional efficacy in pediatric patients, 28 days to 12 years of age, was assessed by changes in triglyceride concentrations and fatty acid parameters.

Pediatric Study 1 enrolled 152 preterm and term neonates (birth up to 28 days) and 9 patients ranging in age from 29 to 153 days. Patients were treated with either SMOFlipid (n=83) or a soybean oil lipid emulsion (n=78). A total of 119 patients (61 SMOFlipid; 58 comparator) received study treatment for ≥14 days. A total of 25 patients received SMOFlipid for ≥29 days; 5 patients received SMOFlipid for the maximum study duration of 78-84 days.

Pediatric Studies 2 and 3 enrolled 60 and 84 preterm neonates, respectively, who were treated with either SMOFlipid or a soybean oil lipid emulsion (72 neonates in each group). The median treatment duration for SMOFlipid group was 12 days in Pediatric Study 2 and 7 days in Pediatric Study 3.

Pediatric Study 4 enrolled 13 patients 5 months to <2 years of age and 15 patients 2 to 11.5 years of age. Patients were treated with either SMOFlipid (n=15) or a soybean oil lipid emulsion (n=13) with a median treatment duration of 27 days.

In Pediatric Studies 1, 2 and 3, which enrolled neonates, SMOFlipid-treated patients showed increases in the median body weight, height/length, and head circumference (which was measured in Studies 1 and 3) comparable to the soybean oil lipid emulsion-treated patients. Mean triglyceride levels from baseline to the final assessment in Pediatric Studies 1, 2, and 3 were variable in these neonates, but overall differences between groups were not considered clinically relevant. Mean triglyceride levels in Pediatric Study 4 were variable, but remained within the normal range.

16 HOW SUPPLIED/STORAGE AND HANDLING

SMOFlipid is a sterile lipid injectable emulsion with a lipid content of 0.2 gram/mL available in Flexible Containers in the following sizes:

Product Code | Unit of Sale | Strength | Each
830307310 | NDC 63323-820-00 Unit of 10 | 20 grams/100 mL (0.2 grams/mL) | NDC 63323-820-01 100 mL single-dose Bag
830307312 | NDC 63323-820-12 Unit of 20 | 20 grams/100 mL (0.2 grams/mL) | NDC 63323-820-02 100 mL single-dose Bag
830570310 | NDC 63323-820-74 Unit of 10 | 50 grams/250 mL (0.2 grams/mL) | NDC 63323-820-04 250 mL single-dose Bag
830820310 | NDC 63323-820-50 Unit of 12 | 100 grams/500 mL (0.2 grams/mL) | NDC 63323-820-03 500 mL single-dose Bag
830920310 | NDC 63323-820-10 Unit of 6 | 200 grams/1000 mL (0.2 grams/mL) | NDC 63323-820-05 1000 mL Pharmacy Bulk Package Bag

Store below 25°C (77°F). Avoid excessive heat. Do not freeze. If accidentally frozen, discard container. Store in overpouch until ready for use.

SMOFlipid 100 mL, 250 mL and 500 mL single-dose Flexible Containers.

After removing the overpouch, infuse immediately. If not used immediately, the product should be stored at 2°C to 8°C (36°F to 46°F) for no longer than 24 hours. After removal from storage, infuse within 12 hours when using a Y-connector or within 24 hours if used as part of an admixture [see Dosage and Administration (2.2)].

SMOFlipid 1000 mL Pharmacy Bulk Package

Use the Pharmacy Bulk Package immediately for admixing after removal from overpouch. If not used immediately, the product should be stored for no longer than 24 hours at 2°C to 8°C (36°F to 46°F). After removal from storage, and once the closure is penetrated, use Pharmacy Bulk Package contents within 4 hours [see Dosage and Administration (2.2)].

Admixtures

Infuse admixtures containing SMOFlipid immediately. If not used immediately, admixtures should be stored at 2°C to 8°C (36°F to 46°F) for no longer than 24 hours. After removal from storage, infuse within 24 hours [see Dosage and Administration (2.2)].

Protect the admixed PN solution from light [see Dosage and Administration (2.2)].

17 PATIENT COUNSELING INFORMATION

When initiating SMOFlipid administration, discuss the following information:

Clinical Decompensation with Rapid Infusion of Intravenous Lipid Emulsion in Neonates and Infants

Inform caregivers that acute respiratory distress and death may occur in neonates and infants after rapid infusion of intravenous lipid emulsions. If SMOFlipid is infused at home, instruct caregivers not to exceed the maximum infusion rate [see Warnings and Precautions (5.1)].

Parenteral Nutrition-Associated Liver Disease and Other Hepatobiliary Disorders

Inform patients and caregivers that use of parenteral nutrition may result in parenteral nutrition- associated liver disease and/or other hepatobiliary disorders [see Warnings and Precautions (5.2)].

Hypersensitivity Reactions

Inform patients and caregivers that SMOFlipid may cause hypersensitivity reactions, including anaphylaxis. If SMOFlipid is infused at home, instruct patients or caregivers to stop the infusion of SMOFlipid immediately and seek medical attention if they experience signs or symptoms of a hypersensitivity reaction, such as rapid or weak heartbeat, feeling faint, difficulty in breathing or swallowing, vomiting, nausea, headache, sweating, dizziness, hives, rash, itching, flushing, dizziness, fever, or chills [see Warnings and Precautions (5.3)].

Infections

Inform patients and caregivers that patients who receive SMOFlipid are at risk of infection. If SMOFlipid is infused at home, instruct patients or caregivers to ensure aseptic techniques are used for the preparation and administration of SMOFlipid and to monitor for signs and symptoms of infection [see Warnings and Precautions (5.4)].

Fat Overload Syndrome

Inform patients and caregivers that fat overload syndrome has been reported with the use of intravenous lipid emulsions. If SMOFlipid is infused at home, instruct patients or caregivers to stop SMOFlipid if signs or symptoms of fat overload syndrome occur [see Warnings and Precautions (5.5)].

Refeeding Syndrome

If the patient is severely malnourished, inform patients and caregivers that administering parenteral nutrition including SMOFlipid may result in refeeding syndrome. [see Warnings and Precautions (5.6)].

Hypertriglyceridemia

Inform patients and caregivers about the risks of hypertriglyceridemia with SMOFlipid use [see Warnings and Precautions (5.7)].

Aluminum Toxicity

Inform patients and caregivers that prolonged PN administration in patients with renal impairment, including preterm neonates, may result in aluminum reaching toxic levels associated with central nervous system and bone toxicity [see Warnings and Precautions (5.8)].

Essential Fatty Acid Deficiency

Inform patients and caregivers that cases of EFAD with the use of SMOFlipid have been reported in adults and pediatric patients in the postmarketing period [see Warnings and Precautions (5.9)].

Preparation and Administration Instructions

If it is acceptable for a patient or caregiver to administer SMOFlipid at home, then provide recommendations on how to prepare, add compatible additives (when appropriate), administer, and store SMOFlipid [see Dosage and Administration (2.1, 2.2)].

Manufactured by:

Uppsala, Sweden
Fresenius Kabi, Oxalert, and SMOFlipid are registered trademarks of Fresenius Kabi, www.fresenius-kabi.com/us
451418F

PACKAGE LABEL

PACKAGE LABEL - PRINCIPAL DISPLAY – SMOFlipid ®100 mL Bag Label

SMOFlipid ®

(lipid injectable emulsion, USP), 20%

20 grams/100 mL (0.2 grams/mL)

For intravenous use.

100 mL

Energy: 200 kcal per 100 mL

Rx only

NDC 63323-820-01

PACKAGE LABEL

PACKAGE LABEL - PRINCIPAL DISPLAY – SMOFlipid ®100 mL Bag Label

SMOFlipid ®

(lipid injectable emulsion, USP), 20%

20 grams/100 mL (0.2 grams/mL)

For intravenous use.

100 mL

Energy: 200 kcal per 100 mL

Rx only

NDC 63323-820-02

PACKAGE LABEL

PACKAGE LABEL - PRINCIPAL DISPLAY – SMOFlipid ®250 mL Bag Label

SMOFlipid ®

(lipid injectable emulsion, USP), 20%

50 grams/250 mL (0.2 grams/mL)

For intravenous use.

250 mL

Energy: 500 kcal per 250 mL

Rx only

NDC 63323-820-04

PACKAGE LABEL

PACKAGE LABEL - PRINCIPAL DISPLAY – SMOFlipid ®500 mL Bag Label

SMOFlipid ®

(lipid injectable emulsion, USP), 20%

100 grams/500 mL (0.2 grams/mL)

For intravenous use.

500 mL

Energy: 1000 kcal per 500 mL

Rx only

NDC 63323-820-03

PACKAGE LABEL

PACKAGE LABEL - PRINCIPAL DISPLAY – SMOFlipid ®1000 mL Bag Label

SMOFlipid ®

(lipid injectable emulsion, USP), 20%

200 grams/1000 mL (0.2 grams/mL)

Pharmacy Bulk Package.

Not for Direct Infusion

For intravenous use.

1000 mL

Energy: 2000 kcal per 1000 mL

Rx only

NDC 63323-820-05